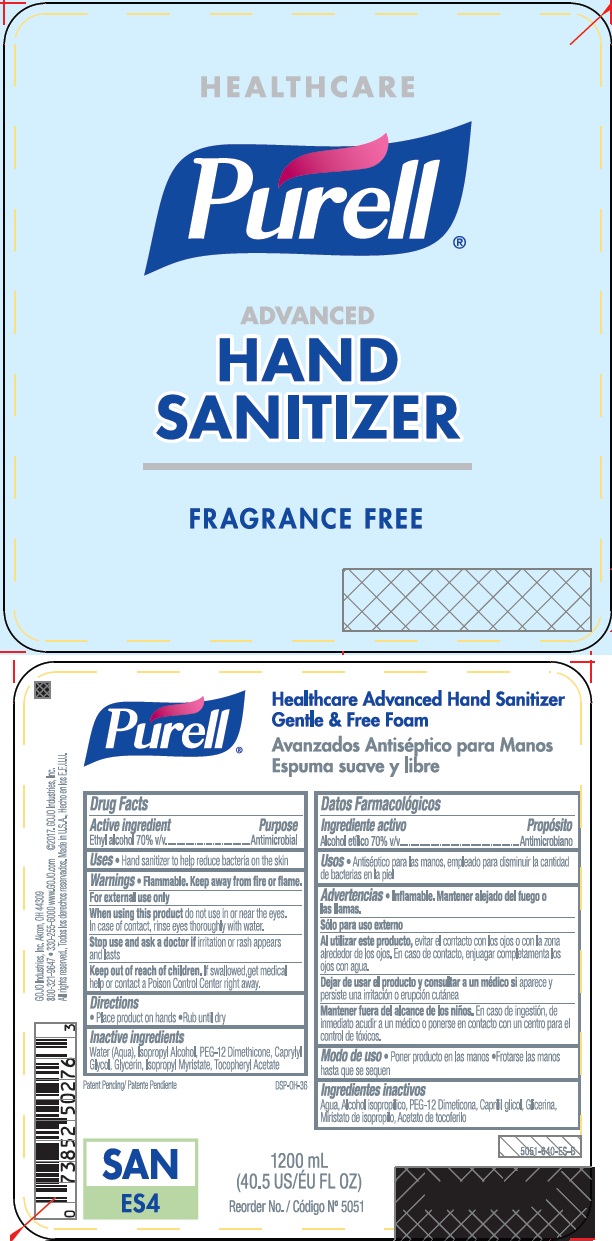 DRUG LABEL: PURELL Healthcare Advanced Hand Sanitizer Gentle and Free Foam
NDC: 21749-822 | Form: LIQUID
Manufacturer: GOJO Industries, Inc.
Category: otc | Type: HUMAN OTC DRUG LABEL
Date: 20251219

ACTIVE INGREDIENTS: ALCOHOL 0.7 mL/1 mL
INACTIVE INGREDIENTS: WATER; ISOPROPYL ALCOHOL; CAPRYLYL GLYCOL; GLYCERIN; ISOPROPYL MYRISTATE; .ALPHA.-TOCOPHEROL ACETATE, D-

PURELL Healthcare Advanced Hand Sanitizer Gentle & Free Foam

Active ingredient

Ethyl alcohol 70% v/v

Purpose

Antimicrobial

Uses

- Hand sanitizer to help reduce bacteria on the skin that cause disease
- Recommended for repeated use

Warnings

Flammable. Keep away from fire or flame.

For external use only

WHEN USING

When using this productdo not use in or near the eyes. In case of contact, rinse eyes thoroughly with water.

Stop use and ask a doctor ifirritation or rash appears and lasts

Keep out of reach of children.If swallowed, get medical help or contact a Poison Control Center right away.

Directions

- Place enough product in your palm to thoroughly cover your hands
- Run hands together briskly until dry
- Children under 6 years of age should be supervised when using this product.

Inactive ingredients

Water (Aqua), Isopropyl Alcohol, PEG-12 Dimethicone, Caprylyl Glycol, Glycerin, Isopropyl Myristate, Tocopheryl Acetate